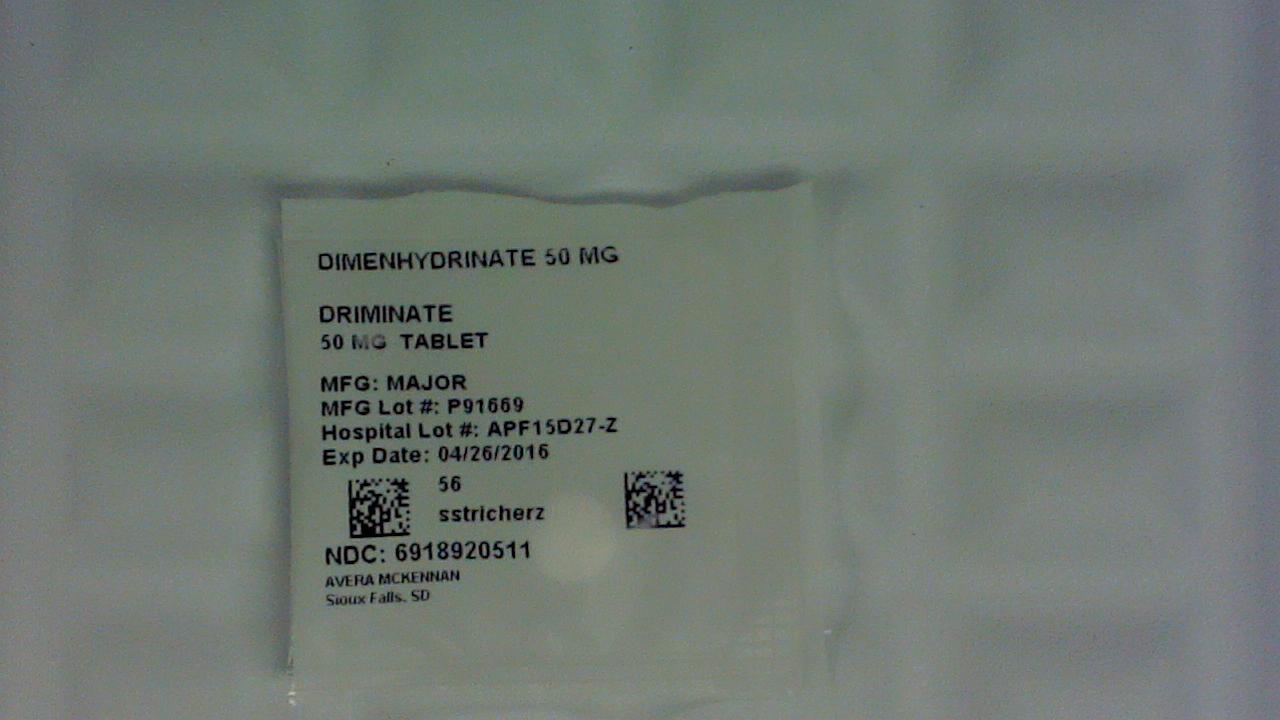 DRUG LABEL: Driminate
NDC: 69189-2051 | Form: TABLET
Manufacturer: Avera McKennan Hospital
Category: otc | Type: HUMAN OTC DRUG LABEL
Date: 20160112

ACTIVE INGREDIENTS: DIMENHYDRINATE 50 mg/1 1
INACTIVE INGREDIENTS: CROSCARMELLOSE SODIUM; CALCIUM PHOSPHATE, DIBASIC, ANHYDROUS; MAGNESIUM STEARATE; CELLULOSE, MICROCRYSTALLINE; STEARIC ACID

Active ingredient (in each tablet)

Dimenhydrinate 50 mg

Purpose

Antiemetic

Uses

for the prevention and treatment of nausea, vomiting, or dizziness associated with motion sickness

Warnings

Do not use

for children under 2 years of age unless directed by a doctor.

Ask a doctor before use if you have

- a breathing problem such as emphysema or chronic bronchitis
- glaucoma
- difficulty in urination due to an enlargement of the prostate gland

Ask a doctor or pharmacist before use if you are

taking sedatives or tranquilizers.

When using this product

- marked drowsiness may occur
- avoid alcoholic drinks
- alcohol, sedatives, and tranquilizers may increase drowsiness
- use caution when driving a motor vehicle or operating machinery

If pregnant or breast-feeding,

ask a health professional before use.

Keep out of reach of children.

In case of overdose, get medical help or contact a Poison Control Center (1-800-222-1222) right away.

Directions

- to prevent motion sickness, the first dose should be taken one-half to one hour before starting activity
- adults and children 12 years of age and over: 1 to 2 tablets every 4-6 hours; not to exceed 8 tablets in 24 hours, or as directed by a doctor
- children 6 to under 12 years of age: 1/2 to 1 tablet every 6-8 hours; not to exceed 3 tablets in 24 hours, or as directed by a doctor
- children 2 to under 6 years of age: 1/2 tablet every 6-8 hours; not to exceed 1 1/2 tablets in 24 hours, or as directed by a doctor

Other information

- store at 25ºC (77ºF); excursions permitted between 15º-30ºC (59º-86ºF)
- protect from moisture
- see end flap for expiration date and lot number

Inactive ingredients

croscarmellose sodium, dicalcium phosphate, magnesium stearate, microcrystalline cellulose, silica gel, stearic acid

Questions or comments?

(800) 616-2471